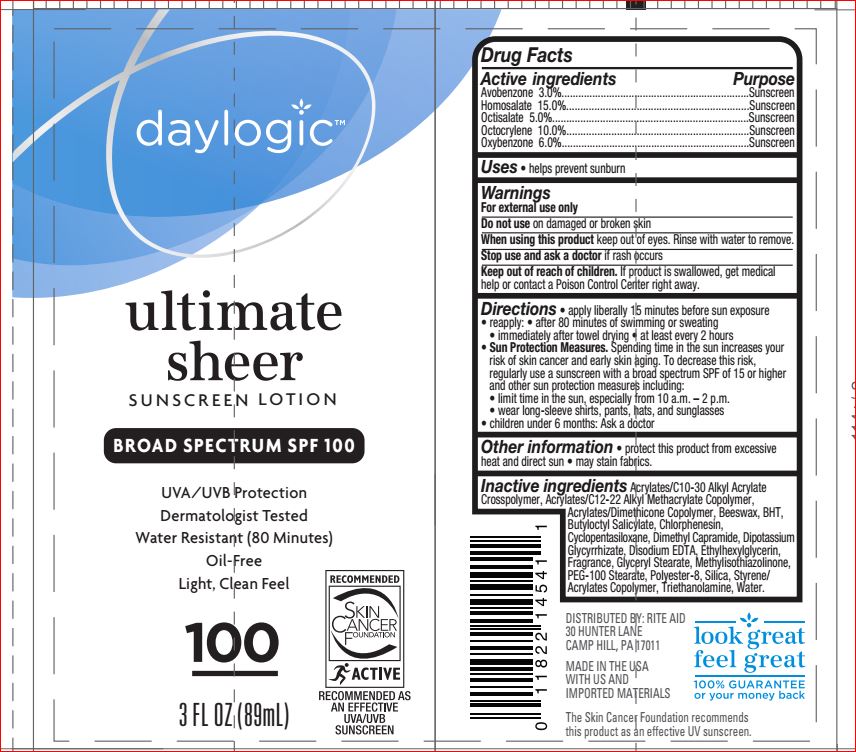 DRUG LABEL: Ultimate Sheer Sunscreen SPF 100
NDC: 11822-1112 | Form: LOTION
Manufacturer: Rite Aid
Category: otc | Type: HUMAN OTC DRUG LABEL
Date: 20171024

ACTIVE INGREDIENTS: Avobenzone 3 g/100 mL; Homosalate 15 g/100 mL; Octisalate 5 g/100 mL; Octocrylene 10 g/100 mL; Oxybenzone 6 g/100 mL
INACTIVE INGREDIENTS: YELLOW WAX; BUTYLATED HYDROXYTOLUENE; Butyloctyl Salicylate; Chlorphenesin; CYCLOMETHICONE 5; Dimethyl Capramide; GLYCYRRHIZINATE DIPOTASSIUM; EDETATE DISODIUM; Ethylhexylglycerin; GLYCERYL MONOSTEARATE; Methylisothiazolinone; PEG-100 Stearate; POLYESTER-8 (1400 MW, CYANODIPHENYLPROPENOYL CAPPED); SILICON DIOXIDE; TROLAMINE; Water; CARBOMER COPOLYMER TYPE B (ALLYL PENTAERYTHRITOL CROSSLINKED); BUTYL ACRYLATE/C16-C20 ALKYL METHACRYLATE/METHACRYLIC ACID/METHYL METHACRYLATE COPOLYMER; METHACRYLATE/METHOXY PEG-10 MALEATE/STYRENE COPOLYMER

Drug Facts

Active ingredients Purpose

Avobenzone - 3.00% Sunscreen
Homosalate - 15.00% Sunscreen
Octisalate - 5.00% Sunscreen
Octocrylene - 10.00% Sunscreen
Oxybenzone - 6.00% Sunscreen

Uses

Helps prevent sunburn • if used as directed with other sun protection measures (see Directions), decreases the risk of skin cancer and early skin aging caused by the sun

Warnings For external use only

Do not use on damage or broken skin

When using this product keep out of eyes. Rinse with water to remove.

Stop use and ask a doctor if rash occurs

KEEP OUT OF REACH OF CHILDREN

Keep out of reach of the children. If swallowed, get medical help or contact a Poison Control Center right away

Directions

• apply liberally 15 minutes before sun exposure
• reapply:
- after 80 minutes of swimming or sweating
- immediately after towel drying
- at least every 2 hours
• Sun Protection Measures. Spending time in the sun increases your risk of skin cancer and early skin aging. To decrease this risk, regularly use a sunscreen SPF of 15 or higher and other sun protection measures including:
- limit time in the sun, especially from 10 a.m. – 2 p.m.
- wear long sleeve shirts, pants, hats, and sunglasses
• children under 6 month: Ask a doctor

Inactive ingredients

Acrylates/C10-30 Alkyl Acrylate Crosspolymer, Acrylates/C12-22 Alkyl Methacrylate Copolymer, Acrylates/Dimethicone Copolymer, Beeswax, BHT, Butyloctyl Salicylate, Chlorphenesin, Cyclopentasiloxane, Dimethyl Capramide, Dipotassium Glycyrrhizate, Disodium EDTA, Ethylhexylglycerin, Fragrance, Glyceryl Stearate, Methylisothiazolinone, PEG-100 Stearate, Polyester-8, Silica, Styrene/Acrylates Copolymer, Triethanolamine, Water

Other information

• protect this product from excessive heat and direct sun • may stain fabrics.